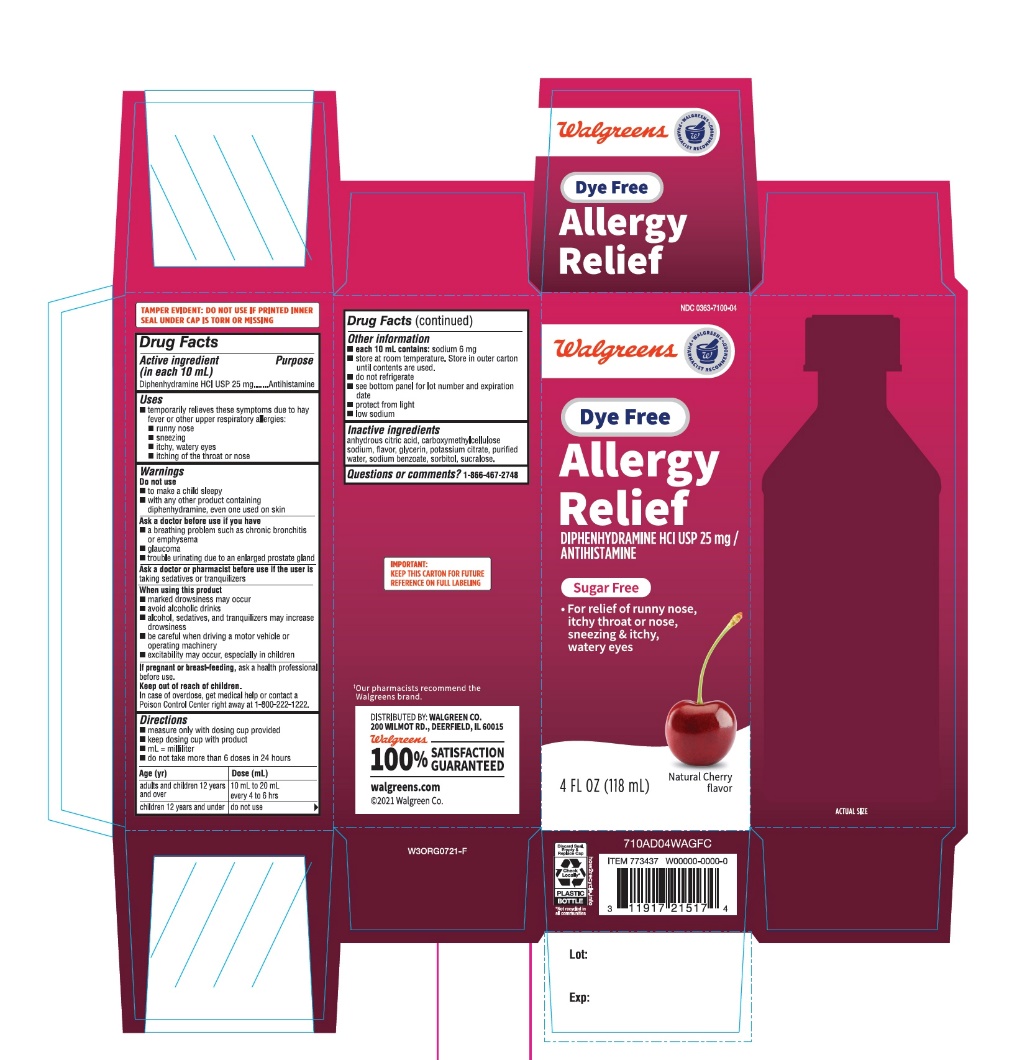 DRUG LABEL: Adult Allergy Relief

NDC: 0363-7100 | Form: SOLUTION
Manufacturer: WALGREEN COMPANY
Category: otc | Type: HUMAN OTC DRUG LABEL
Date: 20251125

ACTIVE INGREDIENTS: DIPHENHYDRAMINE HYDROCHLORIDE 25 mg/10 mL
INACTIVE INGREDIENTS: ANHYDROUS CITRIC ACID; CARBOXYMETHYLCELLULOSE SODIUM, UNSPECIFIED; CHERRY; GLYCERIN; POTASSIUM CITRATE; WATER; SODIUM BENZOATE; SORBITOL; SUCRALOSE

Dye-Free Adult’s Allergy Relief Oral Solution

Drug Facts

Active ingredient [in each 10 mL]
Diphenhydramine HCl, USP 25 mg

Purpose

Antihistamine

Uses

- temporarily relieves these symptoms due to hay fever or other upper respiratory allergies:
  - sneezing
  - itchy, watery eyes
  - runny nose
  - itching of the nose or throat

Warnings

Do not use

- to make a child sleepy
- with any other product containing diphenhydramine, even one used on skin

Ask a doctor before use if you have

- a breathing problem such as chronic bronchitis
- glaucoma
- a sodium-restricted diet
- trouble urinating due to enlarged prostate

Ask a doctor or pharmacist before use if you aretaking sedatives or tranquilizers

When using this product

- marked drowsiness may occur
- avoid alcoholic drinks
- alcohol, sedatives and tranquilizers may increase drowsiness
- be careful when driving a motor vehicle or operating machinery
- excitability may occur, especially in children

If pregnant or breast feeding,ask a health professional before use

Keep out of reach of children

In case of overdose, get medical help or contact a Poison Control Center (1-800-222-1222) right away.

Directions

- measure only with dosing cup provided
- Keep dosing cup with product
- mL = milliliter
- do not take more than 6 doses in 24 hours

Age (yr) | Dose (mL)
Adult and children 12 years and older | 10 mL to 20 mL (2 to 4 tsp) every 4 to 6 hrs
Children under 12 years | Do not use

Other information

- each 10 mL contains:sodium 6 mg
- store at room temperature. Store in outer carton until contents used
- do not refrigerate
- see bottom panel for lot number and expiration date
- protect from light
- low sodium

Inactive ingredients

anhydrous citric acid, carboxymethylcellulose sodium, flavors, glycerin, potassium citrate, purified water, sodium benzoate, sorbitol, sucralose
Questions or Comments?
1-866-467-2748

Package Label-Principal Display Panel 4 Fl Oz (118 Ml Bottle)

NDC 0363-7100-04
Dye-Free
Adult Allergy Relief
Diphenhydramine HCl| Antihistamine
For Relief of:

- Runny nose
- Itchy, watery eyes
- Sneezing and Itchy Watery Eyes

Sugar Free
Cherry Flavor

Naturally and Artificially Flavored
4 FL OZ (118 mL)

†Our pharmacists recommend the Walgreens brand.

DISTRIBUTED BY: WALGREEN CO.

200 WILMOT RD., DEERFIELD, IL 60015

Walgreens

100% SATISFACTION GURANTEED

Walgreens.com

@2021 Walgreens Co.

IMPORTANT:KEEP THIS CARTON FOR FUTURE REFERENCE ON FULL LABELING.